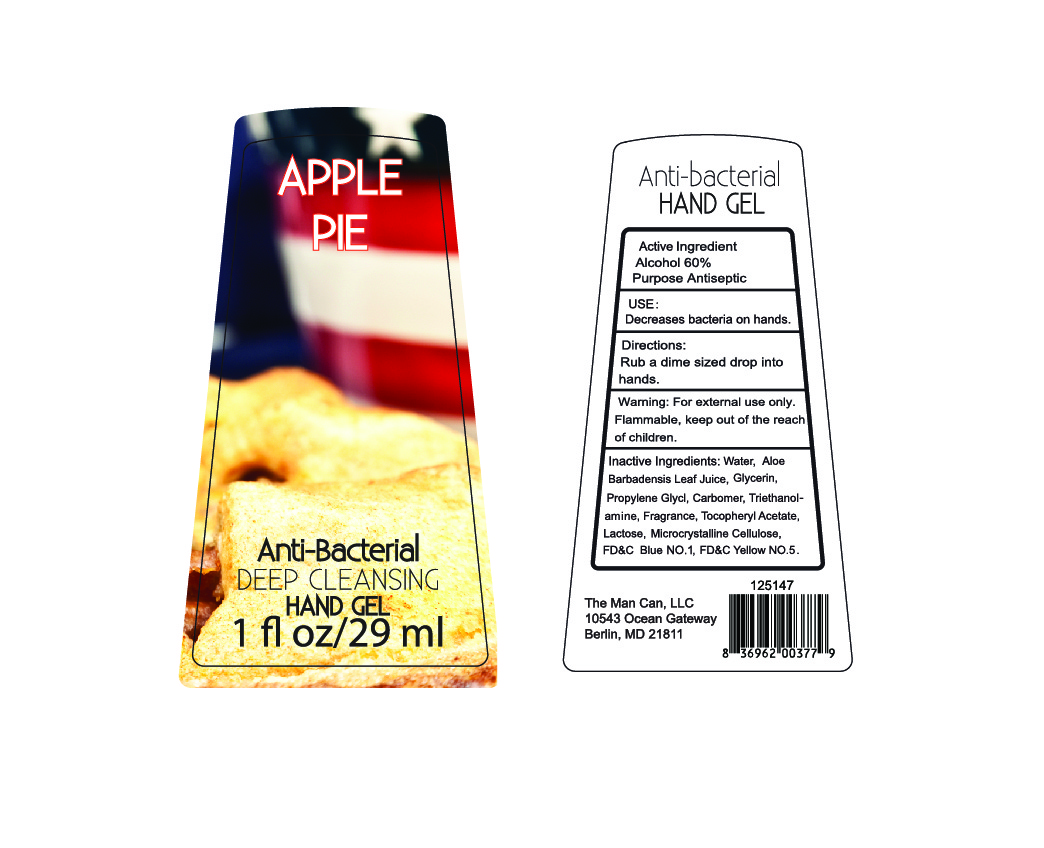 DRUG LABEL: Anti-Bacterial Hand Gel Apple Pie
                
NDC: 59045-1001 | Form: GEL
Manufacturer: The Man Can, LLC
Category: otc | Type: HUMAN OTC DRUG LABEL
Date: 20130710

ACTIVE INGREDIENTS: Alcohol 60 mL/100 mL
INACTIVE INGREDIENTS: WATER; GLYCERIN; PROPYLENE GLYCOL; CARBOMER HOMOPOLYMER TYPE C (ALLYL PENTAERYTHRITOL CROSSLINKED); ALOE; ALOE VERA LEAF; TROLAMINE; .ALPHA.-TOCOPHEROL ACETATE; LACTOSE; CELLULOSE, MICROCRYSTALLINE; FD&C BLUE NO. 1; FD&C YELLOW NO. 5

Active Ingredient

Alcohol 60%

Purpose
Antiseptic

INDICATIONS AND USAGE

Use: Decreases bacteria on hands.

WARNINGS

Warning: For external use only. Flammable.

Keep out of reach of children.

DOSAGE AND ADMINISTRATION

Directions: Rub a dime sized drop into hands

INACTIVE INGREDIENTS:
Water, Aloe Barbadensis Leaf Juice, Glycerin, Propylene Glycol, Carbomer, Triethanolamine, Fragrance, Tocopheryl Acetate, Lactose, Microcrystalline Cellulose, FD&C Blue NO.1, FD&C Yellow NO.5.